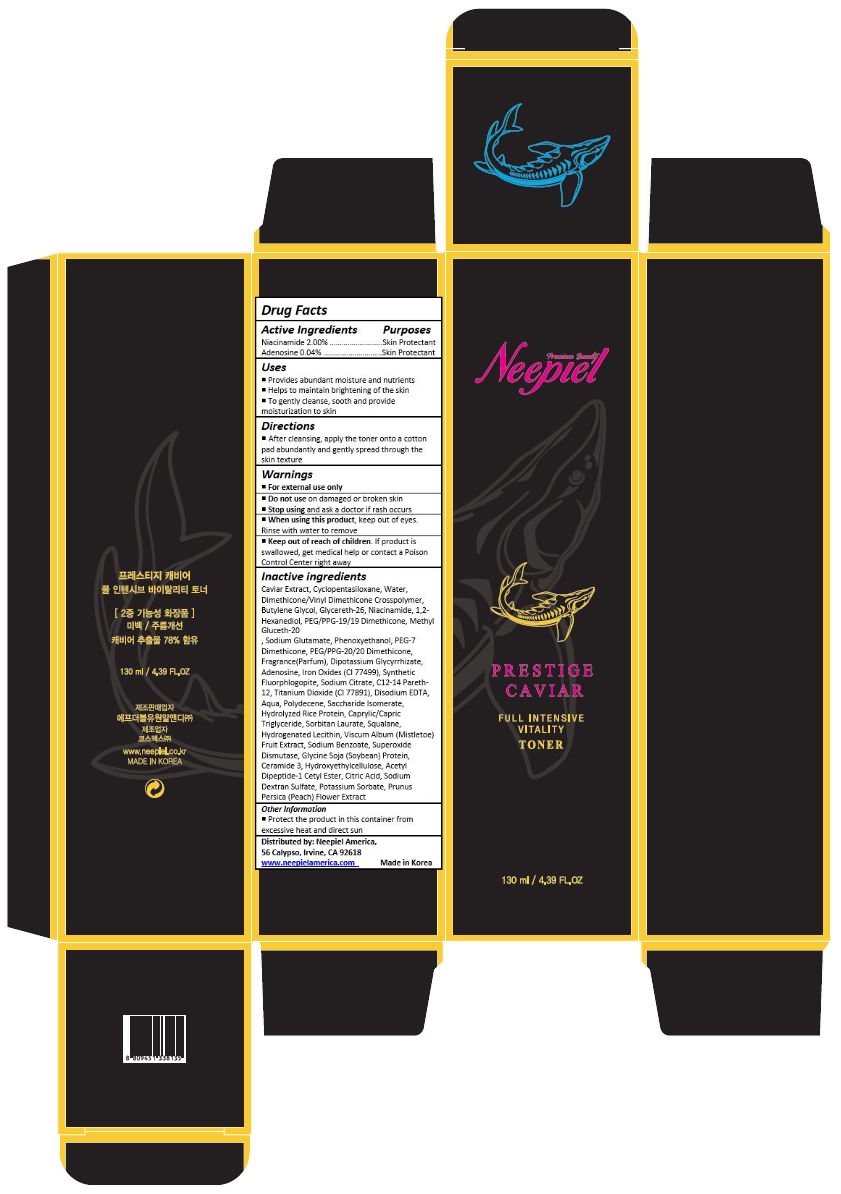 DRUG LABEL: Prestige Caviar Full Intensive Vitality Toner
NDC: 70519-002 | Form: LIQUID
Manufacturer: FW1 R&D_Branch
Category: otc | Type: HUMAN OTC DRUG LABEL
Date: 20170627

ACTIVE INGREDIENTS: NIACINAMIDE 2.6 mg/130 mL; ADENOSINE 0.052 mg/130 mL
INACTIVE INGREDIENTS: CAVIAR, UNSPECIFIED; ALCOHOL; PROPANEDIOL; GLYCERETH-26; FLAX SEED; 1,2-HEXANEDIOL; BETAINE; BUTYLENE GLYCOL DICAPRYLATE/DICAPRATE; WATER; METHYL GLUCETH-20; BIS-PEG-18 METHYL ETHER DIMETHYL SILANE; BUTYLENE GLYCOL; PEG-60 HYDROGENATED CASTOR OIL; PHENOXYETHANOL; HYDROXYETHYL ACRYLATE/SODIUM ACRYLOYLDIMETHYL TAURATE COPOLYMER (100000 MPA.S AT 1.5%); CARBOMER INTERPOLYMER TYPE A (ALLYL SUCROSE CROSSLINKED); OCTYLDODECETH-16; TROMETHAMINE; PHENYL TRIMETHICONE; CARBOXYMETHYLCELLULOSE SODIUM, UNSPECIFIED FORM; EDETATE DISODIUM; ICODEXTRIN; COCOA; GARDENIA JASMINOIDES FRUIT; MALTODEXTRIN; GLYCERIN; HYDROGENATED DIDECENE; SAFFLOWER; SACCHARIDE ISOMERATE; MEDIUM-CHAIN TRIGLYCERIDES; HYDROXYETHYL CELLULOSE (100 MPA.S AT 2%); SORBITAN MONOLAURATE; SQUALANE; HYDROGENATED SOYBEAN LECITHIN; VISCUM ALBUM FRUIT; ACTINIDIA POLYGAMA FRUIT; CERAMIDE NP; ACETYL TYROSYLARGININE CETYL ESTER; SODIUM CITRATE, UNSPECIFIED FORM; CITRIC ACID MONOHYDRATE; POTASSIUM SORBATE; PRUNUS PERSICA FLOWER

Drug Facts

ACTIVE INGREDIENT

Niacinamide 2.00%
Adenosine 0.04%

PURPOSE

Skin Protectant

INDICATIONS AND USAGE

To gently cleanse, sooth and provide moisturization to skin

DOSAGE AND ADMINISTRATION

After washing face, moisten a cotton pad with toner or dispenses onto palm and apply to skin areas where needed, avoid eye areas

WARNINGS

For external use only.
Do not use on damaged or broken skin.
When using this product, keep out of eyes. Rinse with water to remove
Stop using and ask a doctor if rash occurs.

Keep out of reach of children.

If product is swallowed, get medical help or contact a Poison Control Center right away.

INACTIVE INGREDIENT

Caviar Extract, Cyclopentasiloxane, Water, Dimethicone/Vinyl Dimethicone Crosspolymer, Butylene Glycol, Glycereth-26, Niacinamide, 1,2-Hexanediol, PEG/PPG-19/19 Dimethicone, Methyl Gluceth-20
, Sodium Glutamate, Phenoxyethanol, PEG-7 Dimethicone, PEG/PPG-20/20 Dimethicone, Fragrance(Parfum), Dipotassium Glycyrrhizate, Adenosine, Iron Oxides (CI 77499), Synthetic Fluorphlogopite, Sodium Citrate, C12-14 Pareth-12, Titanium Dioxide (CI 77891), Disodium EDTA, Aqua, Polydecene, Saccharide Isomerate, Hydrolyzed Rice Protein, Caprylic/Capric Triglyceride, Sorbitan Laurate, Squalane, Hydrogenated Lecithin, Viscum Album (Mistletoe) Fruit Extract, Sodium Benzoate, Superoxide Dismutase, Glycine Soja (Soybean) Protein, Ceramide 3, Hydroxyethylcellulose, Acetyl Dipeptide-1 Cetyl Ester, Citric Acid, Sodium Dextran Sulfate, Potassium Sorbate, Prunus Persica (Peach) Flower Extract